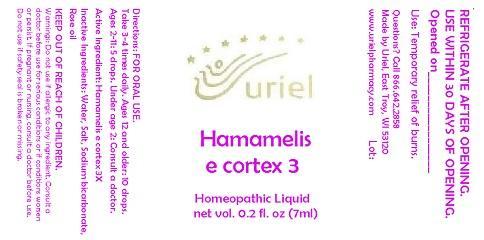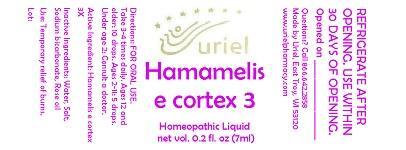 DRUG LABEL: Hamamelis e cortex 3
NDC: 48951-5030 | Form: LIQUID
Manufacturer: Uriel Pharmacy Inc.
Category: homeopathic | Type: HUMAN OTC DRUG LABEL
Date: 20140908

ACTIVE INGREDIENTS: HAMAMELIS VIRGINIANA TOP 3 [hp_X]/1 mL
INACTIVE INGREDIENTS: WATER; SODIUM CHLORIDE; SODIUM BICARBONATE; ROSE OIL

Hamamelis e cortex 3

INDICATIONS AND USAGE

Directions: FOR ORAL USE.

DOSAGE AND ADMINISTRATION

Take 3-4 times daily. Ages 12 and older: 10 drops. Ages 2-11: 5 drops. Under age 2: Consult a doctor.

Active Ingredient: Hamamelis e cortex 3X

Inactive Ingredients: Water, Salt, Sodium bicarbonate, Rose oil

PURPOSE

Use: Temporary relief of burns.

KEEP OUT OF REACH OF CHILDREN.

WARNINGS

Warnings: Do not use if allergic to any ingredient. Consult a doctor before use for serious conditions or if conditions worsen or persist. If pregnant or nursing, consult a doctor before use. Do not use if safety seal is broken or missing.

REFRIGERATE AFTER OPENING. USE WITHIN 30 DAYS OF OPENING.

QUESTIONS

Questions? Call 866.642.2858 Made by Uriel, East Troy, WI 53120 www.urielpharmacy.com